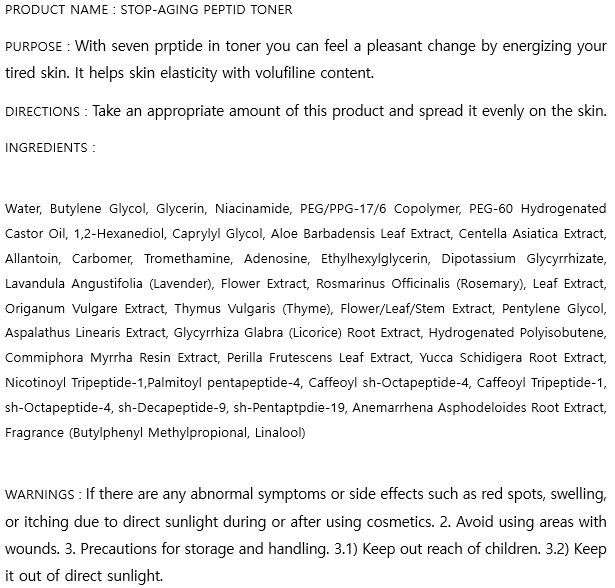 DRUG LABEL: STOP-AGING PEPTIDE TONER
NDC: 74997-0007 | Form: LIQUID
Manufacturer: J&J COMPANY
Category: otc | Type: HUMAN OTC DRUG LABEL
Date: 20201007

ACTIVE INGREDIENTS: NIACINAMIDE 2 g/100 mL; ADENOSINE 0.04 g/100 mL
INACTIVE INGREDIENTS: GLYCERIN; BUTYLENE GLYCOL; WATER

J&J COMPANY - STOP-AGING PEPTIDE TONER

ACTIVE INGREDIENT

Niacinamide, Adenosine

INACTIVE INGREDIENT

Water, Butylene Glycol, Glycerin, Niacinamide, PEG/PPG-17/6 Copolymer, PEG-60 Hydrogenated Castor Oil, 1,2-Hexanediol, Caprylyl Glycol, Aloe Barbadensis Leaf Extract, Centella Asiatica Extract, Allantoin, Carbomer, Tromethamine, Adenosine, Ethylhexylglycerin, Dipotassium Glycyrrhizate, Lavandula Angustifolia (Lavender), Flower Extract, Rosmarinus Officinalis (Rosemary), Leaf Extract, Origanum Vulgare Extract, Thymus Vulgaris (Thyme), Flower/Leaf/Stem Extract, Pentylene Glycol, Aspalathus Linearis Extract, Glycyrrhiza Glabra (Licorice) Root Extract, Hydrogenated Polyisobutene, Commiphora Myrrha Resin Extract, Perilla Frutescens Leaf Extract, Yucca Schidigera Root Extract, Nicotinoyl Tripeptide-1,Palmitoyl pentapeptide-4, Caffeoyl sh-Octapeptide-4, Caffeoyl Tripeptide-1, sh-Octapeptide-4, sh-Decapeptide-9, sh-Pentaptpdie-19, Anemarrhena Asphodeloides Root Extract, Fragrance (Butylphenyl Methylpropional, Linalool)

PURPOSE

With seven peptide in eye cream user can feel a pleasant change by energizing your tired skin. It helps skin elasticity with volufiline content.

keep out of reach of the children

INDICATIONS AND USAGE

Take an appropriate amount of this product and spread it evenly on the skin.

WARNINGS

If there are any abnormal symptoms or side effects such as red spots, swelling, or itching due to direct sunlight during or after using cosmetics. 2. Avoid using areas with wounds. 3. Precautions for storage and handling. 3.1) Keep out reach of children. 3.2) Keep it out of direct sunlight.

DOSAGE AND ADMINISTRATION

for external use only